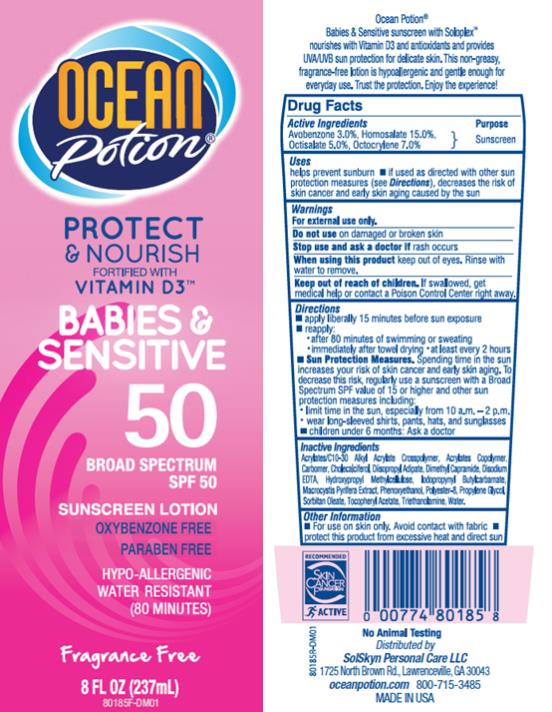 DRUG LABEL: OP Protect and Nourish Babies and Sensitive SPF 50
NDC: 70281-215 | Form: LOTION
Manufacturer: SolSkyn Personal Care LLC
Category: otc | Type: HUMAN OTC DRUG LABEL
Date: 20180215

ACTIVE INGREDIENTS: AVOBENZONE 3 g/100 g; HOMOSALATE 15 g/100 g; OCTISALATE 5 g/100 g; OCTOCRYLENE 7 g/100 g
INACTIVE INGREDIENTS: CARBOMER INTERPOLYMER TYPE A (55000 CPS); CARBOXYPOLYMETHYLENE; CHOLECALCIFEROL; DIISOPROPYL ADIPATE; DIMETHYL CAPRAMIDE; EDETATE DISODIUM ANHYDROUS; HYPROMELLOSES; IODOPROPYNYL BUTYLCARBAMATE; MACROCYSTIS PYRIFERA; PHENOXYETHANOL; POLYESTER-8 (1400 MW, CYANODIPHENYLPROPENOYL CAPPED); PROPYLENE GLYCOL; SORBITAN MONOOLEATE; ALPHA-TOCOPHEROL ACETATE; TROLAMINE; WATER

OP Baby Sensitive Sunscreen Ltn 50

OP Protect & Nourish Babies & Sensitive SPF 50

Active Ingredients

Avobenzone 3.0%

Active Ingredients

Homosalate 15.0%

Active Ingredients

Octisalate 5.0%

Active Ingredients

Octocrylene 7.0%,

Purpose

Sunscreen

Uses

• Helps prevent sunburn.

• If used as directed with other sun protection measures (see Directions), decreases the risk of skin cancer and early skin aging caused by the sun.

Warnings:

• For external use only.

• Keep out of reach of children.

If swallowed, get medical help or contact a Poison Control Center right away.

Directions:

• Apply liberally 15 minutes before sun exposure.

• Re-apply:

• after 80 minutes of swimming or sweating

• immediately after towel drying

• at least every 2 hours

• Sun Protection Measures. Spending time in the sun increases your risk of skin cancer and early skin aging. To decrease this risk, regularly use a sunscreen with a Broad Spectrum SPF value of 15 or higher and other sun protection measures including:

• limit time in the sun, especially from 10 a.m.-2 p.m.

• wear long-sleeved shirts, pants, hats and sunglasses

• Children under 6 months: ask a doctor.

Inactive Ingredients

Acrylates / C10-30 Alkyl Acrylate Crosspolymer, Acrylates Copolymer, Carbomer, Cholecalciferol, Diisopropyl Adipate, Dimethyl Capramide, Disodium EDTA, Hydroxypropyl Methylcellulose, Idopropynyl Butylcarbamate, Macrocystis Pyrifera Extract, Phenoxyethanol, Polyester-8, Propylene Glycol, Sorbitan Oleate, Tocopheryl Acetate, Triethanolamine, Water

Other Information:

• For use on skin only. Avoid contact with fabric.

• Protect this product from excessive heat and direct sun.

PRINCIPAL DISPLAY PANEL

Ocean Potion
Protect
& Nourish
Vitamin D3
Babies &
Sensitive
SPF 50
8 fl oz (237 mL)